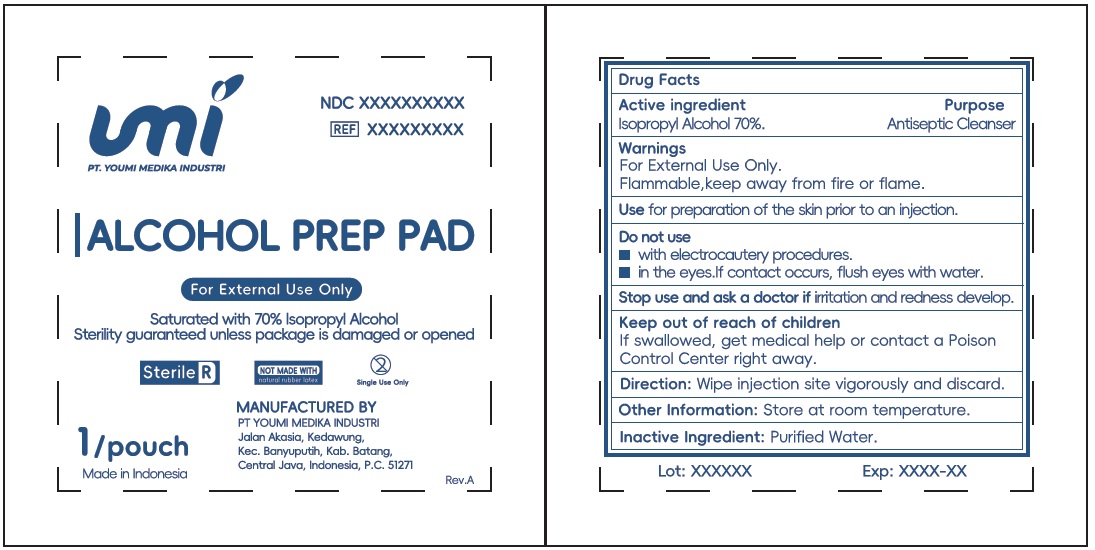 DRUG LABEL: Youmi Alcohol Prep Pad 70 Isopropyl Alcohol
NDC: 87401-000 | Form: LIQUID
Manufacturer: PT YOUMI MEDIKA INDUSTRI
Category: otc | Type: HUMAN OTC DRUG LABEL
Date: 20260209

ACTIVE INGREDIENTS: ISOPROPYL ALCOHOL 70 mL/100 mL
INACTIVE INGREDIENTS: WATER

Youmi Alcohol Prep Pad 70% Isopropyl Alcohol

Active ingredient

Isopropyl Alcohol 70%

Purpose

Antiseptic Cleanser

Use

for preparation of the skin prior to an injection.

Warnings

For External Use Only.
Flammable, keep away from fire or flame.

Do not use

- with electrocautery procedures.
- in the eyes. If contact occurs, flush eyes with water.

Stop use and ask a doctor if

irritation and redness develop.

Keep out of reach of children.

If swallowed, get medical help or contact a Poison Control Center right away.

Directions:

Wipe injection site vigorously and discard.

Other Information:

Store at room temperature.

Inactive Ingredient:

Purified Water.